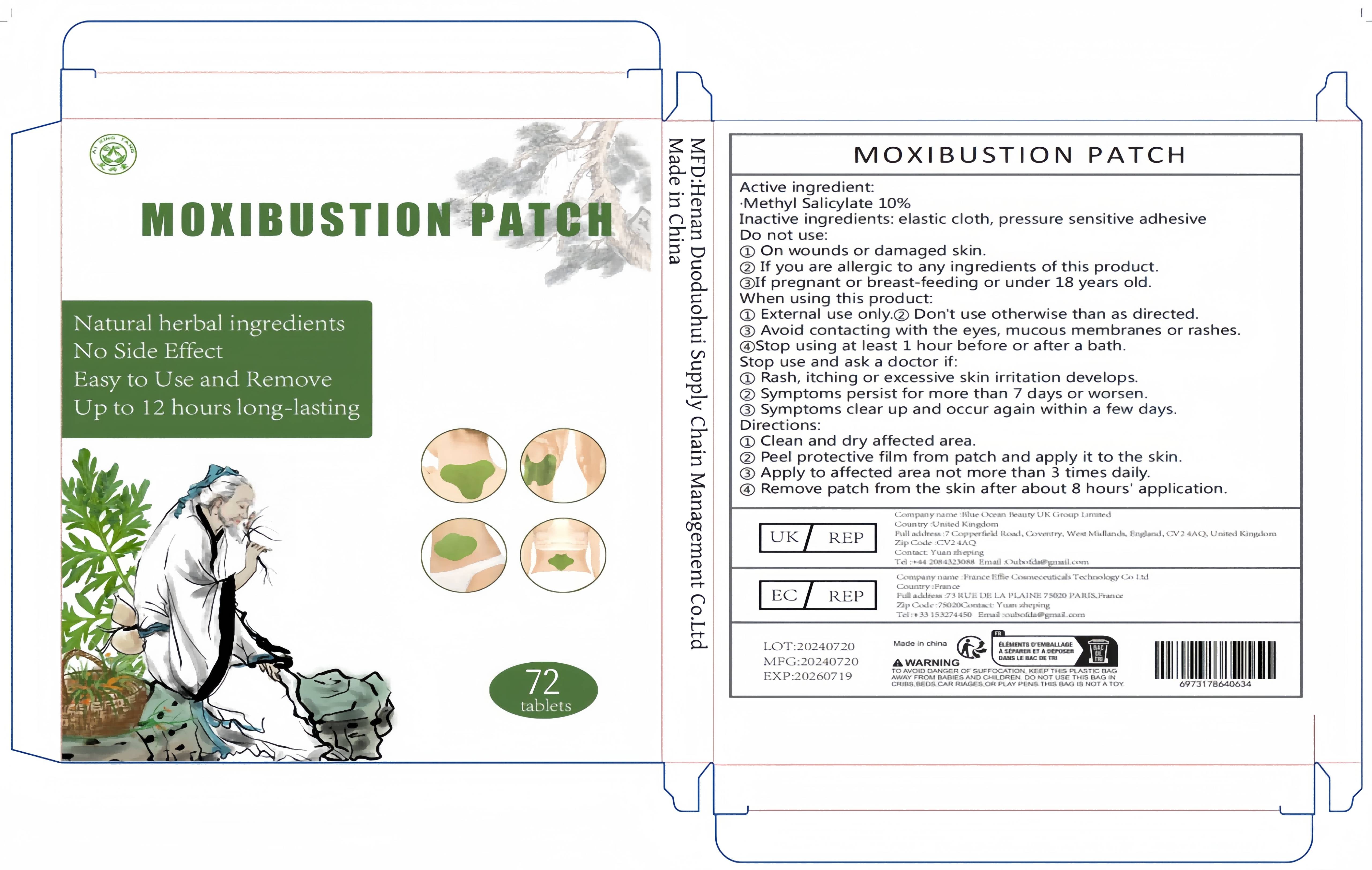 DRUG LABEL: Moxibustion patch
NDC: 84842-002 | Form: PATCH
Manufacturer: Henan Duoduohui Supply Chain Management Co., Ltd.
Category: otc | Type: HUMAN OTC DRUG LABEL
Date: 20241112

ACTIVE INGREDIENTS: ARTEMISIA ARGYI LEAF 10 g/100 g
INACTIVE INGREDIENTS: EUPHORBIA SIEBOLDIANA ROOT; BORNEOL; PANAX NOTOGINSENG TOP; ZINGIBER OFFICINALE WHOLE

Active ingredients

ARTEMISIA ARGYI LEAF 10%

Purpose

Relieve joint pain: Ai Cao Tie is often used to relieve joint pain caused by rheumatism, arthritis, or other reasons.

Improving muscle pain: For problems such as muscle soreness, sprains, strains, etc., mugwort patches can also have a certain soothing effect.

Promote blood circulation: Ai Cao Tie can help improve local blood circulation and promote smooth circulation of qi and blood.

Expelling Cold and Dampness: In traditional Chinese medicine theory, mugwort has the effect of dispelling cold and dampness, and is suitable for discomfort caused by cold and dampness

Uses

①clean and dry affected area.

②Peel protective film from patch and apply it to the skin.

③Apply to affected area not more than 3 times daily.

④Remove patch from the skin after about 8 hours' application.

Warnings

①Rash,itching or excessive skin irritation develops.

②symptoms persist for more than 7 days or worsen.

③Symptoms clearup and occur again within a few days.

Dosage and administration

①External use only.② Don't use otherwise than as directed.

③Avoid contacting with the eyes, mucous membranes or rashes

④Stop using at least 1 hour before or after a bath.

Do not use

①Rash,itching or excessive skin irritation develops.

②symptoms persist for more than 7 days or worsen.

③Symptoms clearup and occur again within a few days.

When using section

①External use only.② Don't use otherwise than as directed.

③Avoid contacting with the eyes, mucous membranes or rashes

④Stop using at least 1 hour before or after a bath.

stop use

① On wounds or damaged skin.

②lf you are allergic to any ingredients of this product.

③lf pregnant or breast-feeding or under 18 years old.

Keep out of reach of children.

Please keep this product out of reach of children. If ingested, seek medical assistance immediately or contact a toxicology center.

Inactive ingredients

ZINGIBER OFFICINALE WHOLE EXTRACT，EUPHORBIA SIEBOLDIANA ROOT，BORNEOL，PANAX NOTOGINSENG TOP